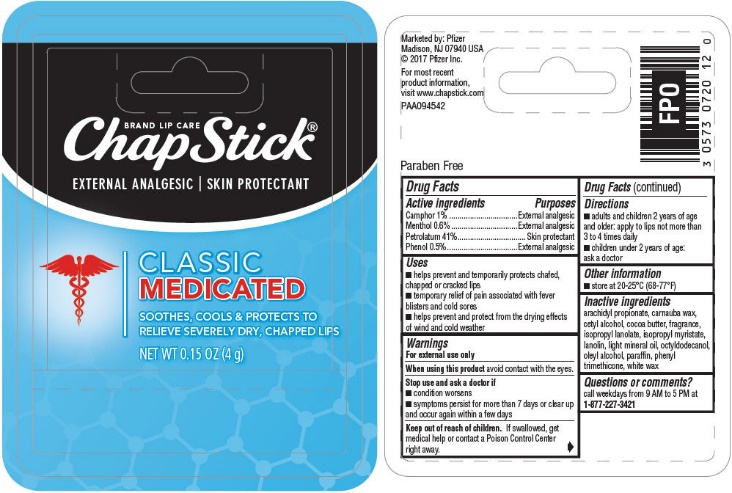 DRUG LABEL: CHAPSTICK MEDICATED
NDC: 0573-0720 | Form: STICK
Manufacturer: Haleon US Holdings LLC
Category: otc | Type: HUMAN OTC DRUG LABEL
Date: 20240123

ACTIVE INGREDIENTS: CAMPHOR (SYNTHETIC) 10 mg/1 g; MENTHOL, UNSPECIFIED FORM 6 mg/1 g; PETROLATUM 410 mg/1 g; PHENOL 5 mg/1 g
INACTIVE INGREDIENTS: ARACHIDYL PROPIONATE; CARNAUBA WAX; CETYL ALCOHOL; COCOA BUTTER; ISOPROPYL MYRISTATE; LANOLIN; LIGHT MINERAL OIL; OCTYLDODECANOL; OLEYL ALCOHOL; PARAFFIN; PHENYL TRIMETHICONE; WHITE WAX

Drug Facts

Active Ingredient

Camphor 1%

Menthol 0.6%

Petrolatum 41%

Phenol 0.5%

Purposes

External analgesic

External analgesic

Skin protectant

External analgesic

Uses

- helps prevent and temporarily protects chafed, chapped or cracked lips
- temporary relief of pain associated with fever blisters and cold sores
- helps prevent and protect from the drying effects of wind and cold weather

Warnings

For external use only

When using this productavoid contact with the eyes.

Stop use and ask a doctor if

- condition worsens
- symptoms persist for more than 7 days or clear up and occur again within a few days

Keep out of reach of children.If swallowed, get medical help or contact a Poison Control Center right away.

Directions

- adults and children 2 years of age and older: apply to lips not more than 3 to 4 times daily
- children under 2 years of age: ask a doctor

Other information

- store at 20-25°C (68-77°F)

Inactive ingredients

arachidyl propionate, carnauba wax, cetyl alcohol, cocoa butter, fragrance, isopropyl lanolate, isopropyl myristate, lanolin, light mineral oil, octyldodecanol, oleyl alcohol, paraffin, phenyl trimethicone, white wax

Questions or comments?

call weekdays from 9 AM to 5 PM at 1-877-227-3421

Additional information

Marketed by: Pfizer

Madison, NJ 07940 USA

© 2017 Pfizer Inc.

For most recent product information, visit www.chapstick.com

Paraben Free

PRINCIPAL DISPLAY PANEL

BRAND LIP CARE

ChapStick®

EXTERNAL ANALGESIC | SKIN PROTECTANT

CLASSIC
MEDICATED

SOOTHES, COOLS & PROTECTS TO
RELIEVE SEVERELY DRY, CHAPPED LIPS

NET WT 0.15 OZ (4 g)